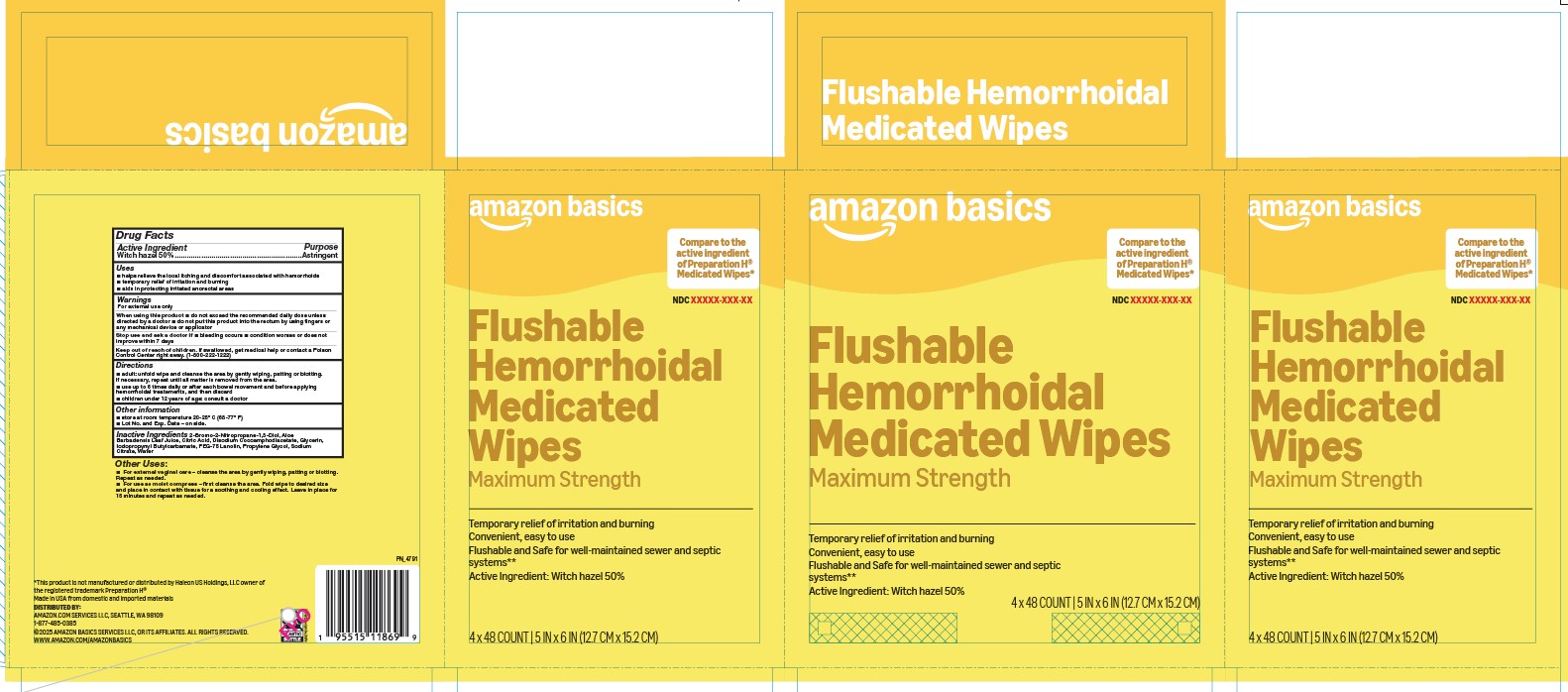 DRUG LABEL: Flushable Hemorrhoidal Medicated Wipes
NDC: 72288-923 | Form: CLOTH
Manufacturer: Amazon.com Services LLC
Category: otc | Type: HUMAN OTC DRUG LABEL
Date: 20251024

ACTIVE INGREDIENTS: WITCH HAZEL 0.5 g/1 1
INACTIVE INGREDIENTS: ANHYDROUS CITRIC ACID; PROPYLENE GLYCOL; SODIUM CITRATE; BRONOPOL; GLYCERIN; ALOE VERA LEAF; DISODIUM COCOAMPHODIACETATE; IODOPROPYNYL BUTYLCARBAMATE; PEG-75 LANOLIN; WATER

Amazon Basics Flushable Hemorrhoidal Medicated Wipes 72288-923

Active ingredient

Witch hazel 50%

Purpose

Astringent

Uses

- helps relieve the local itching and discomfort associated with hemorrhoids
- temporary relief of irritation and burning
- aids in protecting irritated anorectal areas

Warnings

For external use only

When using this product

- do not exceed the recommended daily dosage unless directed by a doctor
- do not put this product into the rectum by using fingers or any mechanical device or applicator

Stop use and ask a doctor if

- bleeding occurs
- condition worsens or does not improve within 7 days

Keep out of reach of children.

If swallowed, get medical help or contact a Poison Control Center right away.(1-800-222-1222)

Directions

- adult: unfold wipe and cleanse the area by gently wiping, patting or blotting. If necessary, repeat until all matter is removed from the area.
- Use up to 6 times daily or after each bowel movement and before applying topical hemorrhoidal treatments, and then discard
- children under 12 years of age: consult a doctor

Other information

store at room temperature 20-25ºC (68-77ºF)

Inactive ingredients

2-Bromo-2-Nitropropane-1,3-Diol, Aloe Barbadensis Leaf Juice, Citric Acid, Disodium Cocoamphodiacetate, Glycerin, Iodopropynyl Butylcarbamate, PEG-75 Lanolin, Propylene Glycol, Sodium Citrate, Water

PACKAGE LABEL

Amazon Basics

Flushable Hemorrhoidal Medicated Wipes

Maximum Strength

Compare to the active ingredient of Preparation H(R) Medicated Wipes*

- Temporary Relief of irritation and burning
- Convenient, easy to use
- Flushable and Safe for Well-maintained sewer and septic Systems**

Active Ingredient: Witch Hazel 50%

2x48 COUNT | 5IN x 6 IN (12CM x 15.2CM)

4x48 COUNT | 5IN x 6 IN (12CM x 15.2CM)

Made in USA from domestic and imported materials

*this product is not manufactured or distributed by Haleon US Holdings, LLC owner of the registered trademark Preparation H

Distributed by Amazon.com services LLC, Seattle WA 98109

1-877-485-0385